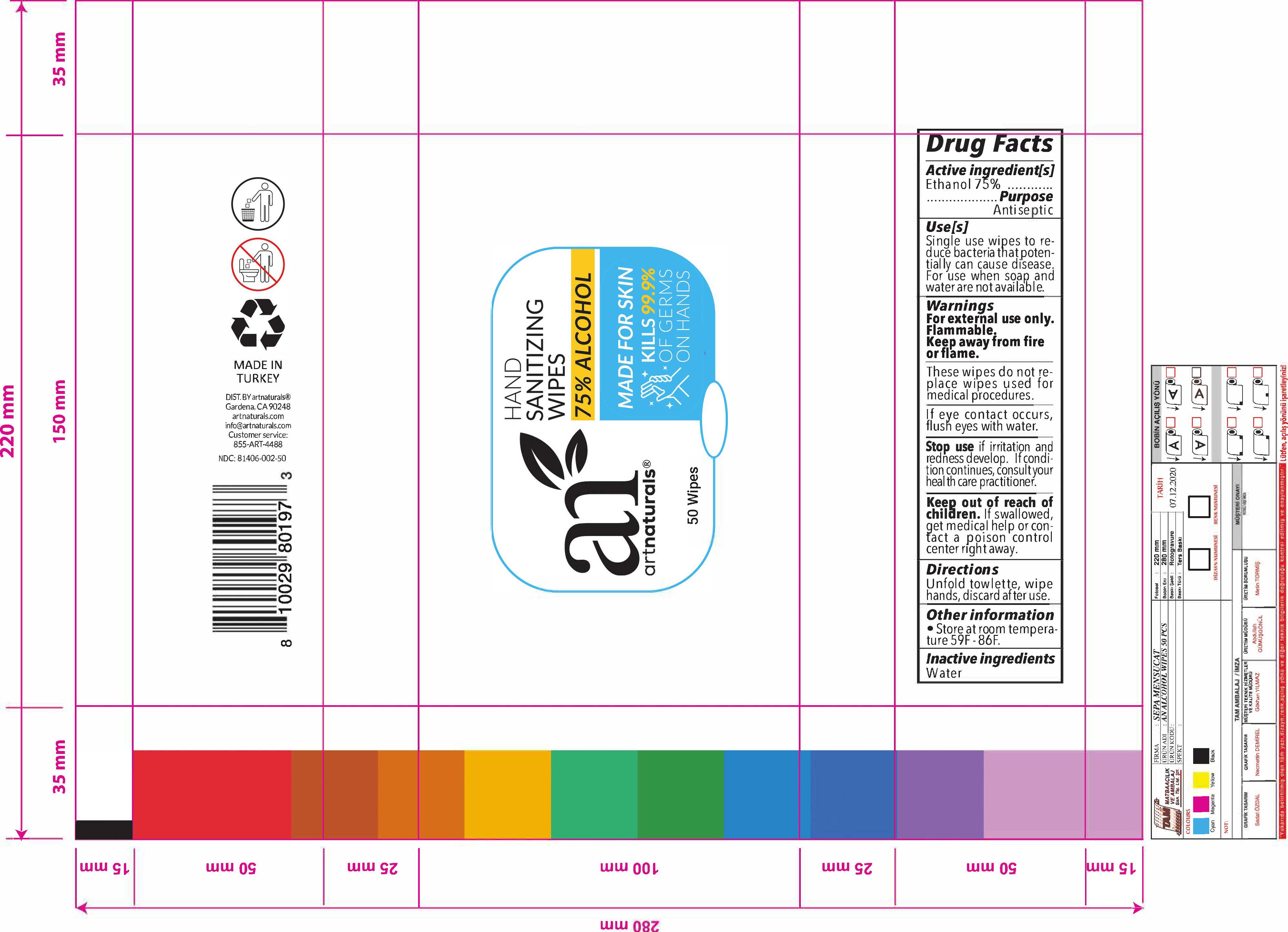 DRUG LABEL: Art Naturals
NDC: 81406-002 | Form: CLOTH
Manufacturer: SEPA MENSUCAT SANAYI VE TICARET ANONIM SIRKETI
Category: otc | Type: HUMAN OTC DRUG LABEL
Date: 20211025

ACTIVE INGREDIENTS: ALCOHOL 75 g/100 g
INACTIVE INGREDIENTS: WATER 25 g/100 g

HAND SANITIZING WIPES

This is a hand sanitizer manufactured according to the Temporary Policy for Preparation of Certain Alcohol-Based Hand Sanitizer Products During the Public Health Emergency (CoViD-19); Guidance for Industry.

The hand sanitizer is manufactured using only the following United States Pharmacopoeia (USP) grade ingredients in the preparation of the product (percentage in final product formulation) consistent with World Health Organization (WHO) recommendations:

1. Isopropyl Alcohol (75%, v/v) in an aqueous solution denatured according to Alcohol and Tobacco Tax and Trade Bureau regulations in 27 CFR part 20.
2. Glycerol (1.45% v/v).
3. Hydrogen peroxide (0.125% v/v).
4. Sterile distilled water or boiled cold water.

The firm does not add other active or inactive ingredients. Different or additional ingredients may impact the quality and potency of the product.

Active Ingredient(s)

Ethanol 75% Purpose: Antiseptic

Purpose

Antiseptic

Use

Single use wipes to reduce bacteria that potentially can cause disease. For use when soap and water are not available

Warnings

For external use only. Flammable. Keep away from heat or flame

Do not use

These wipes do not replace wipes used for medical procedures

WHEN USING

If eye contact occurs flush eyes with water

Stop use if irritation and redness develop. If condition continues, consult your health care practitioner

Keep out of reach of children. If swallowed, get medical help or contact a Poison Control Center right away.

Directions

Unfold towelette, wipe hands, discard after use

Other information

- Store at room Temperature 59-86F

Inactive ingredients

Water

Package Label - Principal Display Panel

50 pcs

200 gr NDC: 81406-002-50

Hand Sanitizing Wipes- 50 pcs NDC: 81406-002-50

Hand Sanitizing Wipes- 50 pcs-200 gr

NDC: 81406-002-50